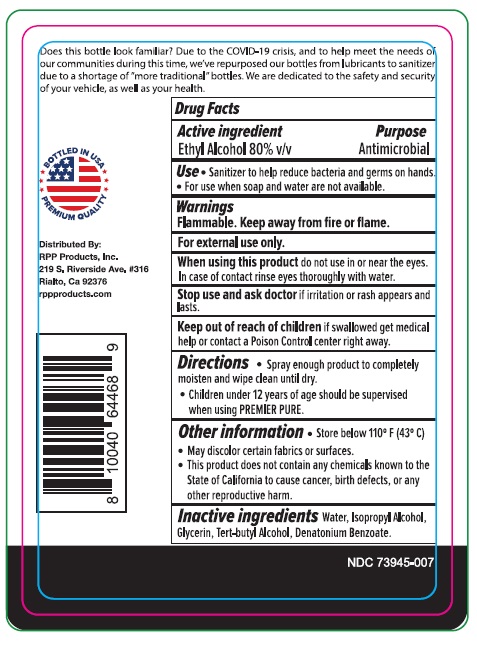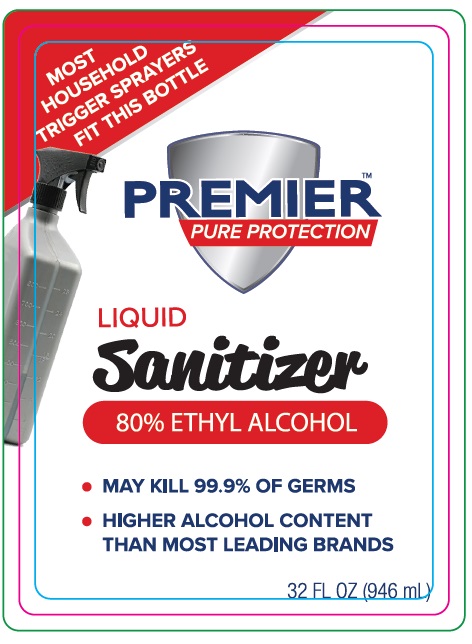 DRUG LABEL: PREMIER PURE PROTECTION
NDC: 73945-007 | Form: LIQUID
Manufacturer: RPP PRODUCTS, INC.
Category: otc | Type: HUMAN OTC DRUG LABEL
Date: 20201123

ACTIVE INGREDIENTS: ALCOHOL 80 mL/100 mL
INACTIVE INGREDIENTS: WATER; ISOPROPYL ALCOHOL; GLYCERIN; TERT-BUTYL ALCOHOL; DENATONIUM BENZOATE

PREMIER PURE PROTECTION

Active ingredient

Ethyl alcohol 80% v/v

Purpose

Antimicrobial

Uses

Sanitizer to help reduce bacteria and germs on hands.

For use when soap and water are not available.

Warnings

Flammable, keep away from fire or flame

For external use only

When using this product

do not use in or near the eyes. In case of contact, rinse eyes thoroughly with water

Stop use and ask doctor if

irritation or rash appears and lasts

Keep out of reach of children.

If swallowed, get medical help right away or contact a Poison Control Center immediately.

Directions

- Spray enough product to completly moisten and wipe clean until dry.
- children under 12 years of age should be supervised when using this PREMIER PURE

Other information

- Store below 110^0 F (43^0C)
- May discolor certain fabrics or surfaces
- This product does not contain any chemicals known to the State of California to cause cancer, birth defects, or any other reproductive harm

Inactive ingredients

Water, Isopropyl Alcohol, Glycerin, Tert-butyl Alcohol, Denatonium Benzoate